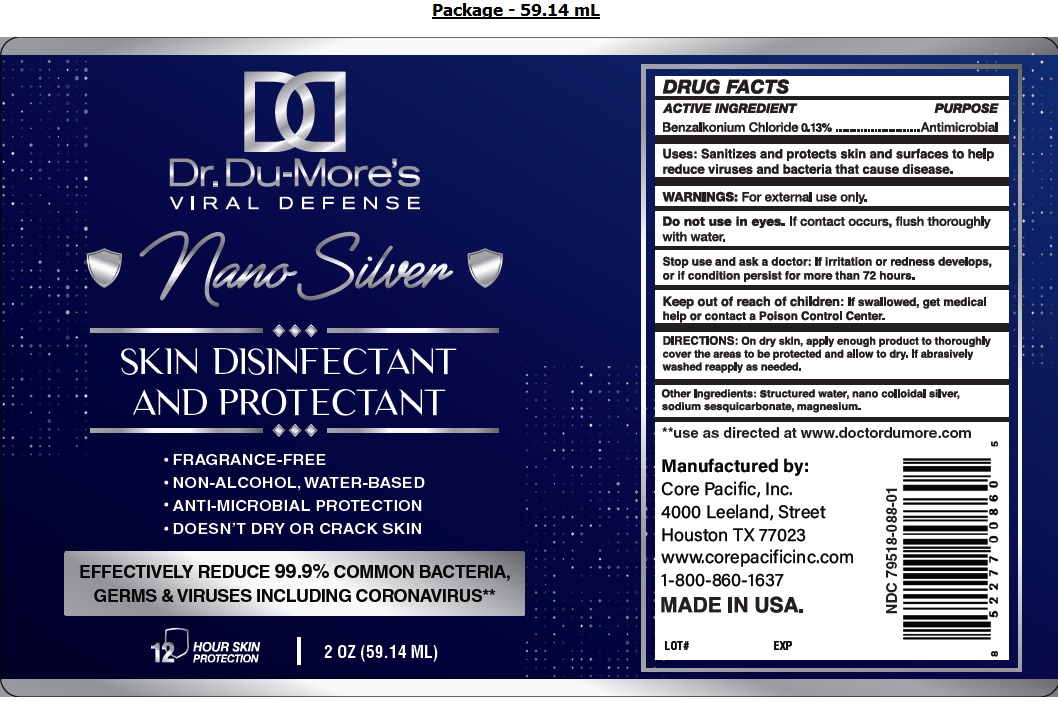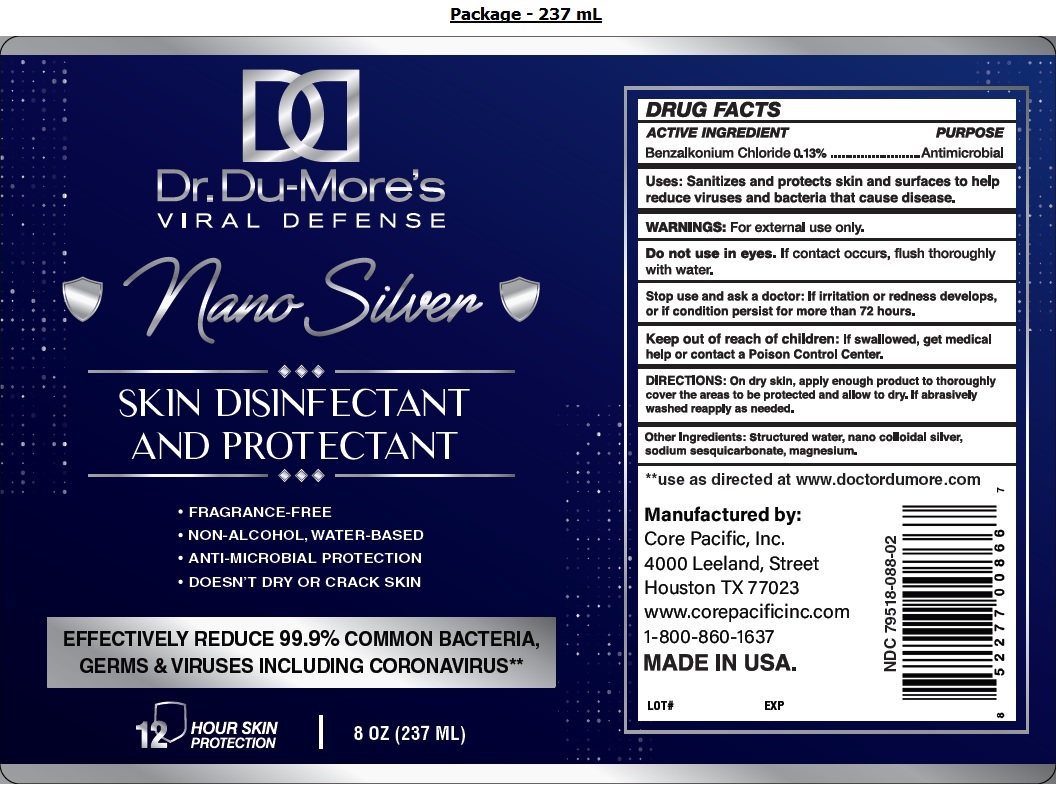 DRUG LABEL: Dr. Du-Mores Viral Defense Nano Silver Skin Disinfectant and Protectant
NDC: 79518-088 | Form: LIQUID
Manufacturer: Core Pacific, Inc.
Category: otc | Type: HUMAN OTC DRUG LABEL
Date: 20201107

ACTIVE INGREDIENTS: BENZALKONIUM CHLORIDE 0.13 g/100 mL
INACTIVE INGREDIENTS: WATER; SILVER; SODIUM SESQUICARBONATE; MAGNESIUM

Dr. Du-More's VIRAL DEFENSE Nano Silver SKIN DISINFECTANT AND PROTECTANT

ACTIVE INGREDIENT

Benzalkonium Chloride 0.13%

PURPOSE

Antimicrobial

Uses:

Sanitizes and protects skin and surfaces to help reduce viruses and bacteria that cause disease.

WARNINGS:

For external use only.

Do not use in eyes. If contact occurs, flush thoroughly with water.

Stop use and ask a doctor: If irritation or redness develops, or if condition persist for more than 72 hours.

Keep out of reach of children: If swallowed, get medical help or contact a Poison Control Center.

DIRECTIONS:

On dry skin, apply enough product to thoroughly cover the areas to be protected and allow to dry. If abrasively washed reapply as needed.

Other Ingredients:

Structured water, nano colloidal silver, sodium sesquicarbonate, magnesium.

• FRAGRANCE-FREE

• NON-ALCOHOL, WATER-BASED

• ANTI-MICROBIAL PROTECTION

• DOESN'T DRY OR CRACK SKIN

EFFECTIVELY REDUCE 99.9% COMMON BACTERIA, GERMS & VIRUSES INCLUDING CORONAVIRUS**

12 HOUR SKIN PROTECTION

**use as directed at www.doctordumore.com

Manufactured by:

Core Pacific, Inc.

4000 Leeland, Street

Houston TX 77023

www.corepacificinc.com

1-800-860-1637

MADE IN USA.